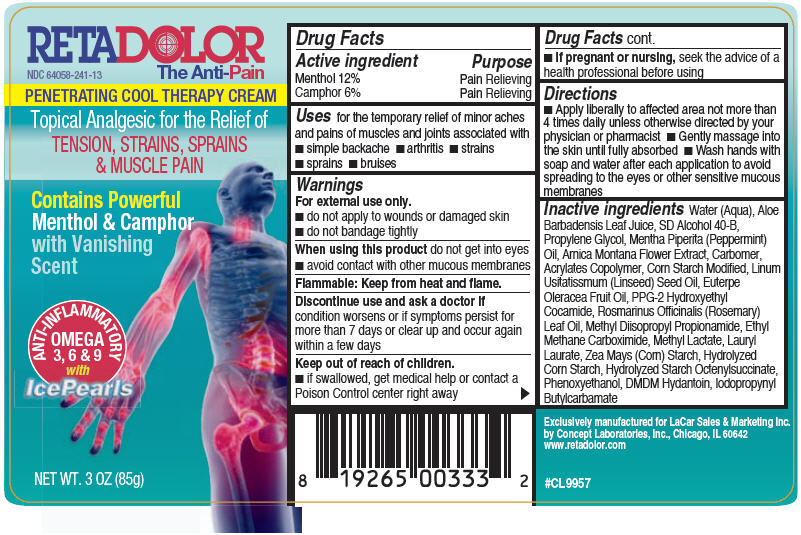 DRUG LABEL: Retadolor 
NDC: 64058-241 | Form: CREAM
Manufacturer: Concept Laboratories, Inc.
Category: otc | Type: HUMAN OTC DRUG LABEL
Date: 20110909

ACTIVE INGREDIENTS: Menthol 10.2 g/85 g; Camphor (Synthetic) 5.1 g/85 g
INACTIVE INGREDIENTS: Water; ALOE VERA LEAF; PROPYLENE GLYCOL; ARNICA MONTANA FLOWER; DMDM HYDANTOIN; PHENOXYETHANOL; IODOPROPYNYL BUTYLCARBAMATE; METHYL DIISOPROPYL PROPIONAMIDE; LAURYL LAURATE; CARBOMER HOMOPOLYMER TYPE C; PEPPERMINT OIL; ALCOHOL; LINSEED OIL; ROSEMARY OIL; ACAI OIL

RETADOLOR
The Anti-Pain
PENETRATING COOL THERAPY CREAM

ACTIVE INGREDIENT

Active ingredient | Purpose
Menthol 12% | Pain Relieving
Camphor 6% | Pain Relieving

Uses

for the temporary relief of minor aches and pains of muscles and joints associated with

- simple backache
- arthritis
- strains
- sprains
- bruises

Warnings

For external use only.

- do not apply to wounds or damaged skin
- do not bandage tightly

When using this product do not get into eyes

- avoid contact with other mucous membranes

Flammable: Keep from heat and flame.

STOP USE

Discontinue use and ask a doctor if condition worsens or if symptoms persist for more than 7 days or clear up and occur again within a few days

Keep out of reach of children.

- if swallowed, get medical help or contact a Poison Control center right away

PREGNANCY OR BREAST FEEDING

- if pregnant or nursing, seek the advice of a health professional before using

Directions

- Apply liberally to affected area not more than 4 times daily unless otherwise directed by your physician or pharmacist
- Gently massage into the skin until fully absorbed
- Wash hands with soap and water after each application to avoid spreading to the eyes or other sensitive mucous membranes

Inactive ingredients

Water (Aqua), Aloe Barbadensis Leaf Juice, SD Alcohol 40-B, Propylene Glycol, Mentha Piperita (Peppermint) Oil, Arnica Montana Flower Extract, Carbomer, Acrylates Copolymer, Corn Starch Modified, Linum Usitatissimum (Linseed) Seed Oil, Euterpe Oleracea Fruit Oil, PPG-2 Hydroxyethyl Cocamide, Rosmarinus Officinalis (Rosemary) Leaf Oil, Methyl Diisopropyl Propionamide, Ethyl Methane Carboximide, Methyl Lactate, Lauryl Laurate, Zea Mays (Corn) Starch, Hydrolyzed Corn Starch, Hydrolyzed Starch Octrenylsuccinate, Phenoxyethanol, DMDM Hydantoin, Iodopropynyl Butylcarbamate

Exclusively manufactured for
LaCar Sales & Marketing Inc.
by Concept Laboratories, Inc.
Chicago, IL 60642
www.retadolor.com
#CL9957

PRINCIPAL DISPLAY PANEL - 85g Bottle Label

RETADOLOR
NDC 64058-241-13
The Anti-Pain

PENETRATING COOL THERAPY CREAM

Topical Analgesic for the Relief of
TENSION, STRAINS, SPRAINS
& MUSCLE PAIN

Contains Powerful
Menthol & Camphor
with Vanishing
Scent

ANTI-INFLAMMATORY
OMEGA
3, 6 & 9
with
IcePearls

NET WT. 3 OZ (85g)